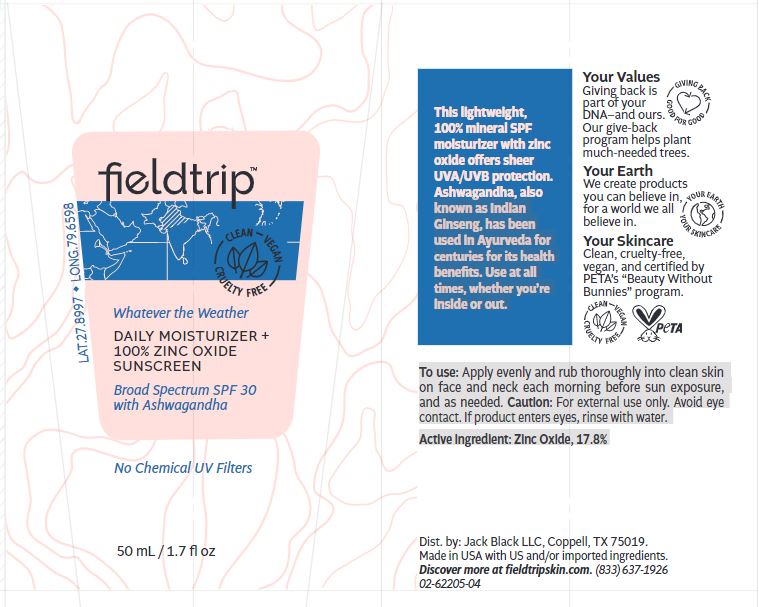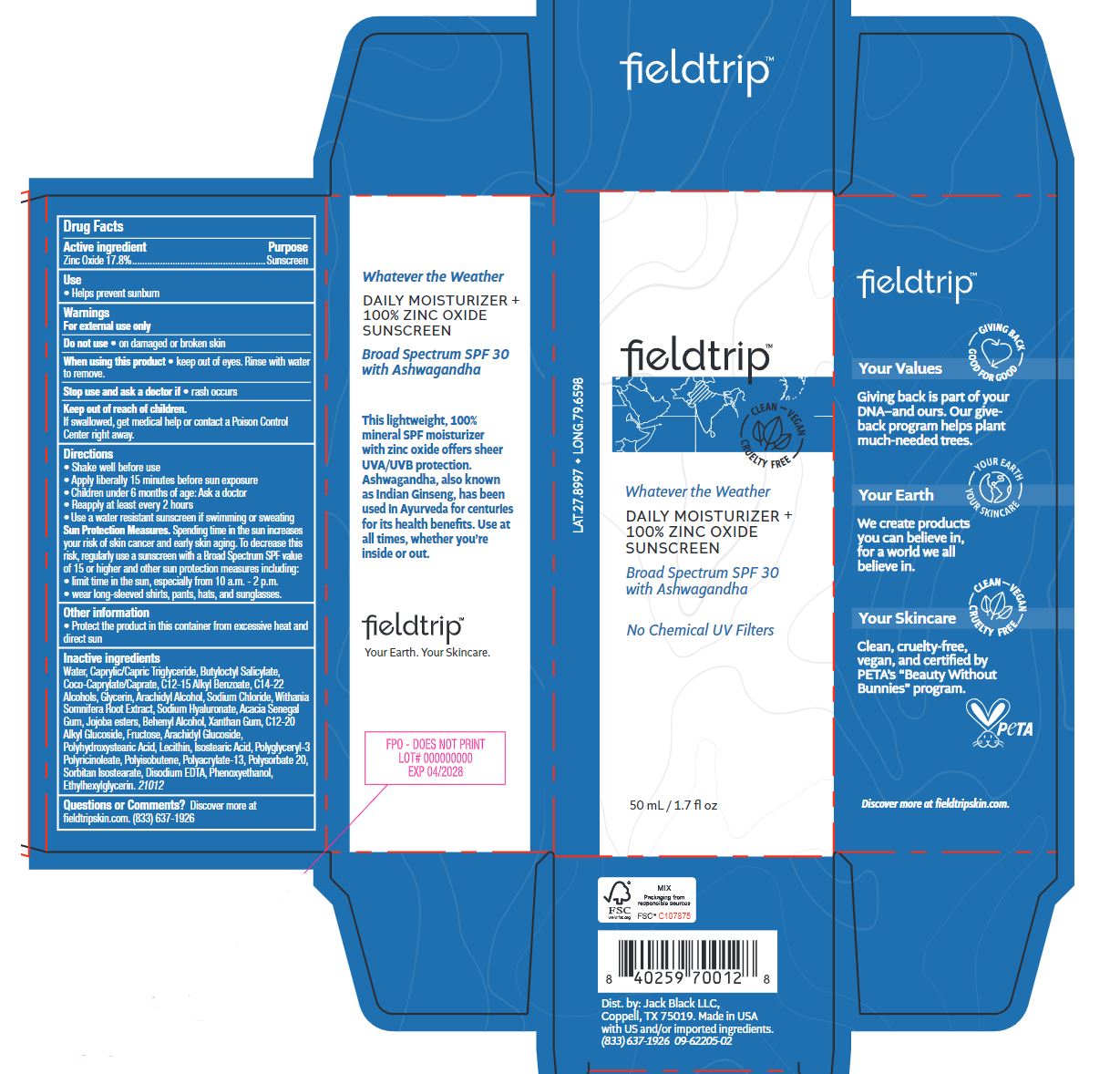 DRUG LABEL: Fieldtrip - Whatever the Weather Daily Moisturizer Zinc Oxide Sunscreen - SPF 30
NDC: 66738-051 | Form: LOTION
Manufacturer: Jack Black L.L.C
Category: otc | Type: HUMAN OTC DRUG LABEL
Date: 20221017

ACTIVE INGREDIENTS: ZINC OXIDE 17.8 g/100 mL
INACTIVE INGREDIENTS: COCO-CAPRYLATE/CAPRATE; C12-20 ALKYL GLUCOSIDE; FRUCTOSE; ARACHIDYL GLUCOSIDE; POLYHYDROXYSTEARIC ACID (2300 MW); POLYGLYCERYL-3 PENTARICINOLEATE; LECITHIN, SOYBEAN; POLYSORBATE 20; ALKYL (C12-15) BENZOATE; EDETATE DISODIUM ANHYDROUS; WATER; C14-22 ALCOHOLS; MEDIUM-CHAIN TRIGLYCERIDES; BUTYLOCTYL SALICYLATE; ARACHIDYL ALCOHOL; SODIUM CHLORIDE; PHENOXYETHANOL; ISOSTEARIC ACID; HYALURONATE SODIUM; POLYISOBUTYLENE (1300 MW); ACACIA; XANTHAN GUM; JOJOBA OIL, RANDOMIZED; DOCOSANOL; GLYCERIN; ETHYLHEXYLGLYCERIN; WITHANIA SOMNIFERA ROOT; SORBITAN ISOSTEARATE

Fieldtrip - Whatever the Weather Daily Moisturizer + 100% Zinc Oxide Sunscreen - SPF 30

Active ingredient

Zinc Oxide 17.8%

Purpose

Sunscreen

Use

• Helps prevent sunburn

Warnings

For external use only

Do not use• on damaged or broken skin

When using this product • keep out of eyes. Rinse with water to remove.

Stop use and ask a doctor if • rash occurs

Keep out of reach of children. If swallowed, get medical help or contact a Poison Control Center right away.

Directions

• Shake well before use

• Apply liberally 15 minutes before sun exposure

• Children under 6 months of age: Ask a doctor

• Reapply at least every 2 hours

• Use a water resistant sunscreen if swimming or sweating Sun Protection Measures. Spending time in the sun increasesyour risk of skin cancer and early skin aging. To decrease this risk, regularly use a sunscreen with a Broad Spectrum SPF valueof 15 or higher and other sun protection measures including:• limit time in the sun, especially from 10 a.m. - 2 p.m. • wear long-sleeved shirts, pants, hats, and sunglasses.

Other information

• Protect the product in this container from excessive heat and direct sun

INACTIVE INGREDIENT

Water, Caprylic/Capric Triglyceride, Butyloctyl Salicylate, Coco-Caprylate/Caprate, C12-15 Alkyl Benzoate, C14-22 Alcohols, Glycerin, Arachidyl Alcohol, Sodium Chloride, Withania Somnifera Root Extract, Sodium Hyaluronate, Acacia Senegal Gum, Jojoba esters, Behenyl Alcohol, Xanthan Gum, C12-20 Alkyl Glucoside, Fructose, Arachidyl Glucoside, Polyhydroxystearic Acid, Lecithin, Isostearic Acid, Polyglyceryl-3 Polyricinoleate, Polyisobutene, Polyacrylate-13, Polysorbate 20, Sorbitan Isostearate, Disodium EDTA, Phenoxyethanol, Ethylhexylglycerin. 21012

Questions or Comments?

Discover more at fieldtripskin.com. (833) 637-1926

PACKAGE LABEL

Fieldtrip - Whatever the Weather Daily Moisturizer + 100% Zinc Oxide Sunscreen - SPF 30